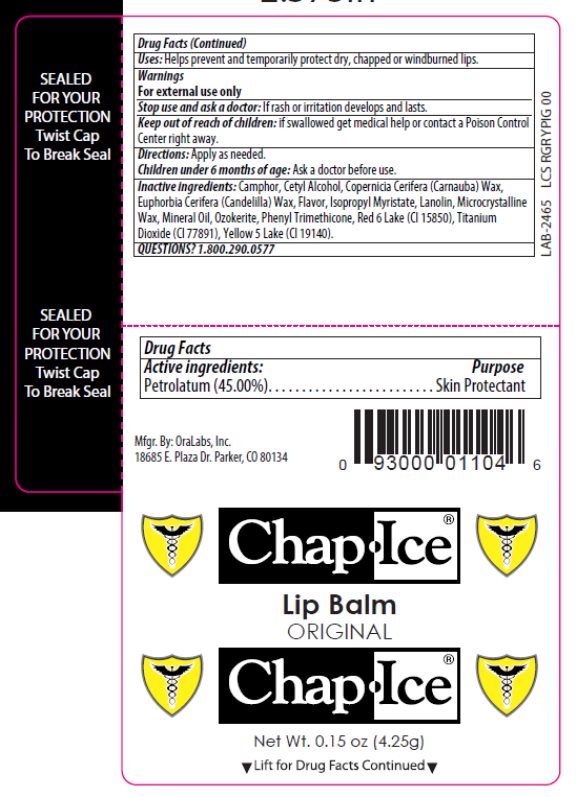 DRUG LABEL: OraLabs ChapIce Original Petrolatum
NDC: 63645-169 | Form: STICK
Manufacturer: OraLabs
Category: otc | Type: HUMAN OTC DRUG LABEL
Date: 20250430

ACTIVE INGREDIENTS: PETROLATUM 45 mg/1 g
INACTIVE INGREDIENTS: LIGHT MINERAL OIL 28 ug/1 g; WHITE WAX 17.5 mg/1 g; MICROCRYSTALLINE WAX 3 mg/1 g; LANOLIN 1 mg/1 g

Drug Facts

Active ingredient

Petrolatum, 45%

Purpose

Skin Protectant

Keep Out of Reach of Children

If swallowed get medical help or contact a Poison Control Center right away.

Uses

Helps prevent and temporarily protect dry, chapped or windburned lips.

Warnings

For external use only. Stop use and ask a doctor if rash or irritation develops and lasts. Children under 6 months of age: Ask a doctor before use.

Directions

Apply as needed.

Inactive Ingredients

Camphor, Cetyl Alcohol, Copernicia Cerifera (Carnauba) Wax, Euphorbia Cerifera (Candelilla) Wax, Flavor, Isopropyl Myristate, Lanolin, Microcrystalline Wax, Mineral Oil, Ozokerite, Phenyl Trimethicone, Red 6 Lake (CI 15850), Titanium Dioxide (CI 77891), Yellow 5 Lake (CI 19140).